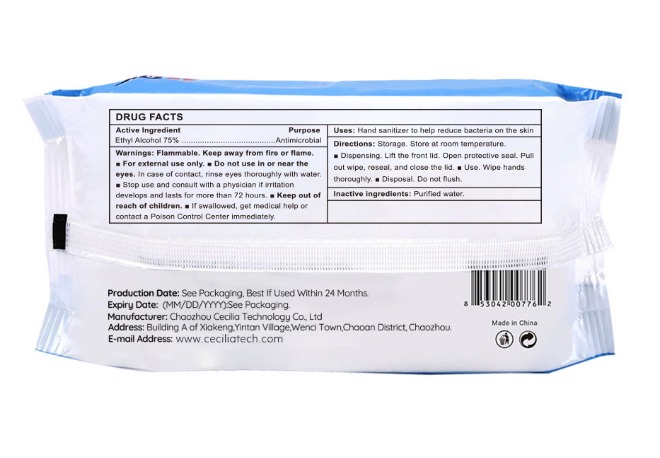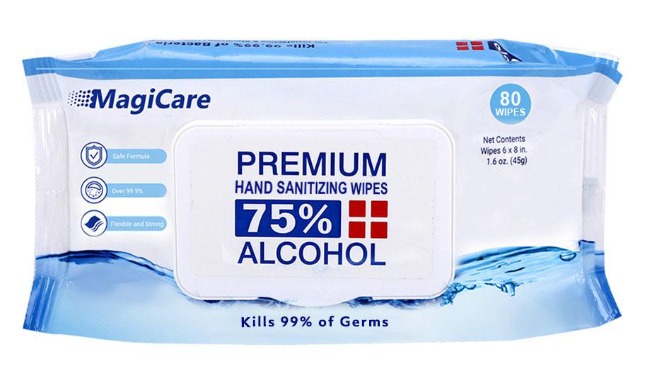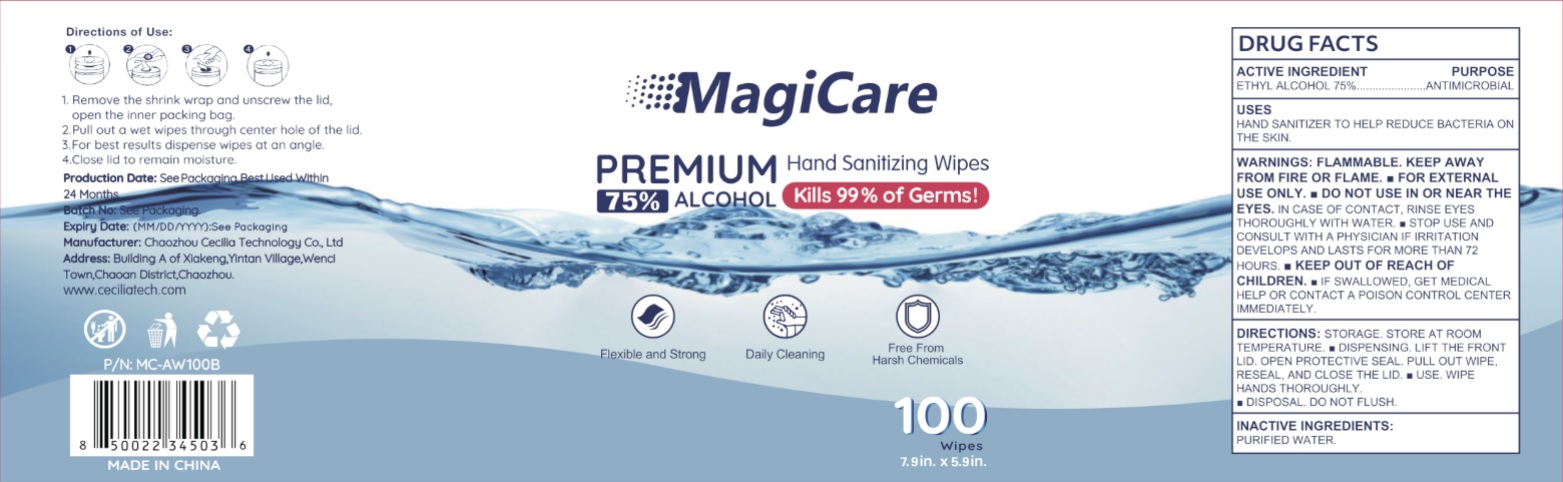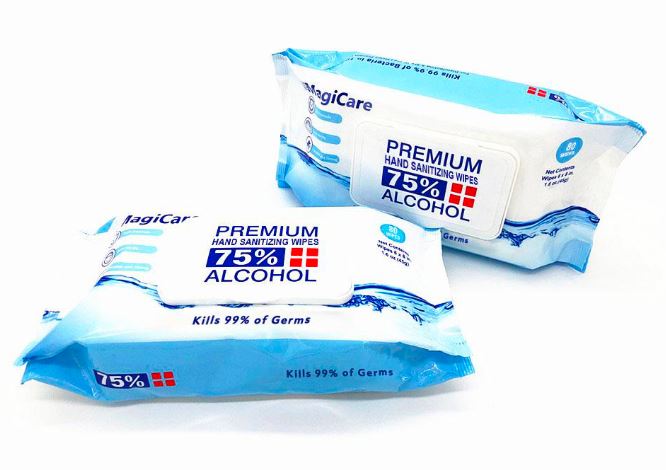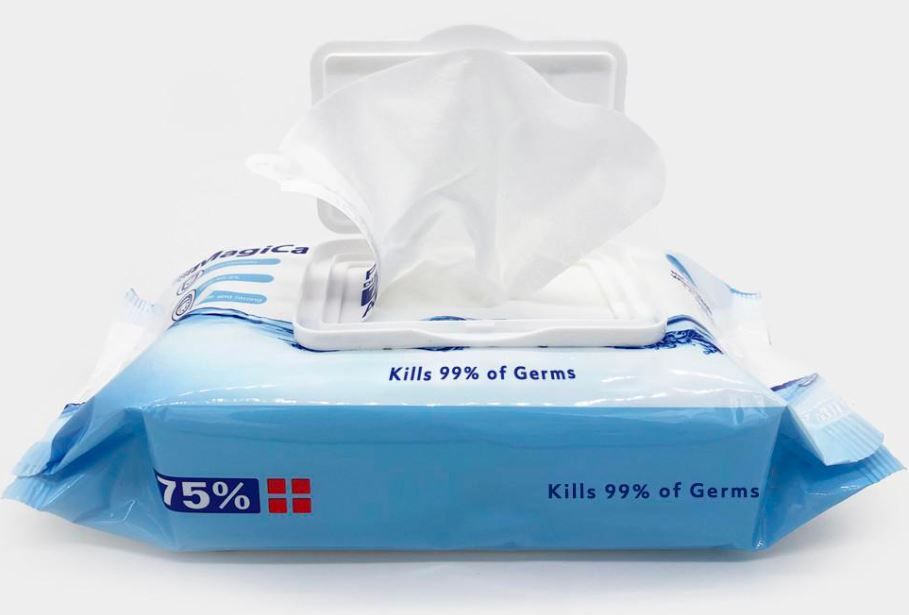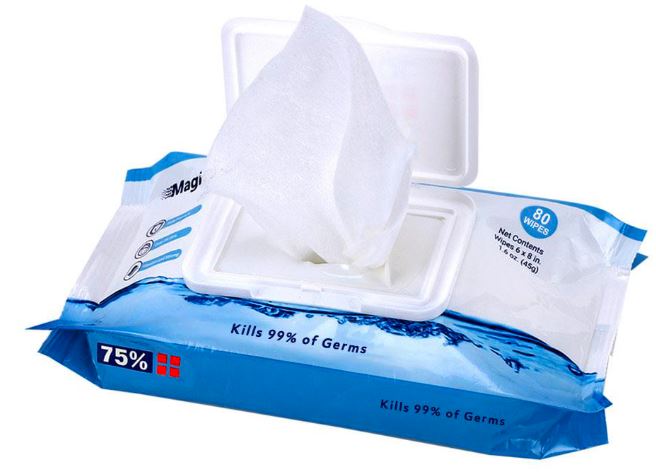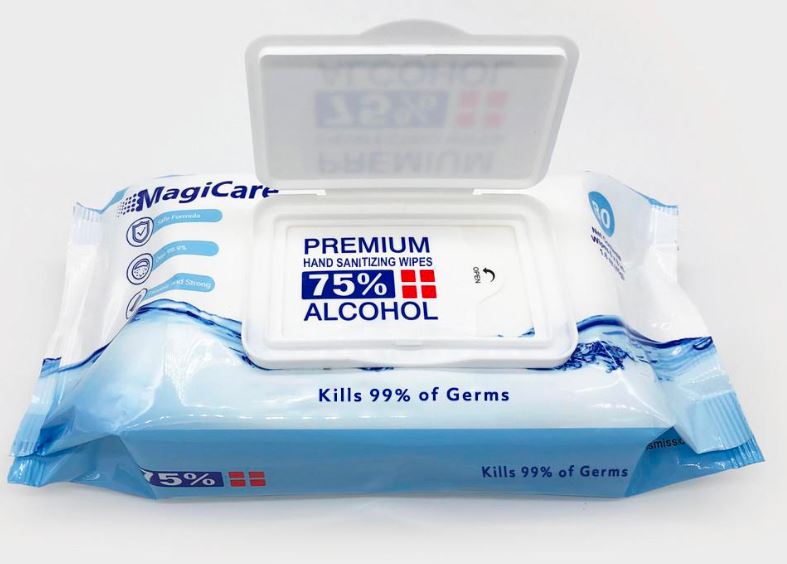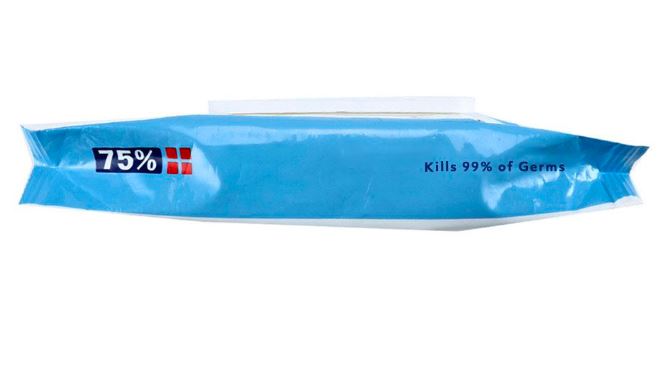 DRUG LABEL: MagiCare Premium Hand Sanitizing Wipes
NDC: 80294-301 | Form: CLOTH
Manufacturer: Chaozhou Cecilia Technology Co., Ltd.
Category: otc | Type: HUMAN OTC DRUG LABEL
Date: 20230306

ACTIVE INGREDIENTS: ALCOHOL 75 g/100 g
INACTIVE INGREDIENTS: WATER

MagiCare Premium Hand Sanitizing Wipes

Active Ingredient

Ethyl Alcohol 75%

Purpose

Antimicrobial

Warnings:

Flammable. Keep away from fire or flame.

• For external use only

• Do not use in or near the eyes.

In case of contact, rinse eyes thoroughly with water.

• Stop use and consult with a physician if irritation develops and lasts for more than 72 hours.

• Keep out of reach of children.

• If swallowed, get medical help or contact a Poison Control Center Immediately.

Uses:

Hand sanitizer to help reduce bacteria on the skin.

Directions:

Storage. Store at room temperature.

• Dispensing. Lift the front lid. Open protective seal. Pull out wipe, reseal, and close the lid. • Use. Wipe hands thoroughly. • Disposal. Do not flush.

Inactive ingredients:

Purified water.